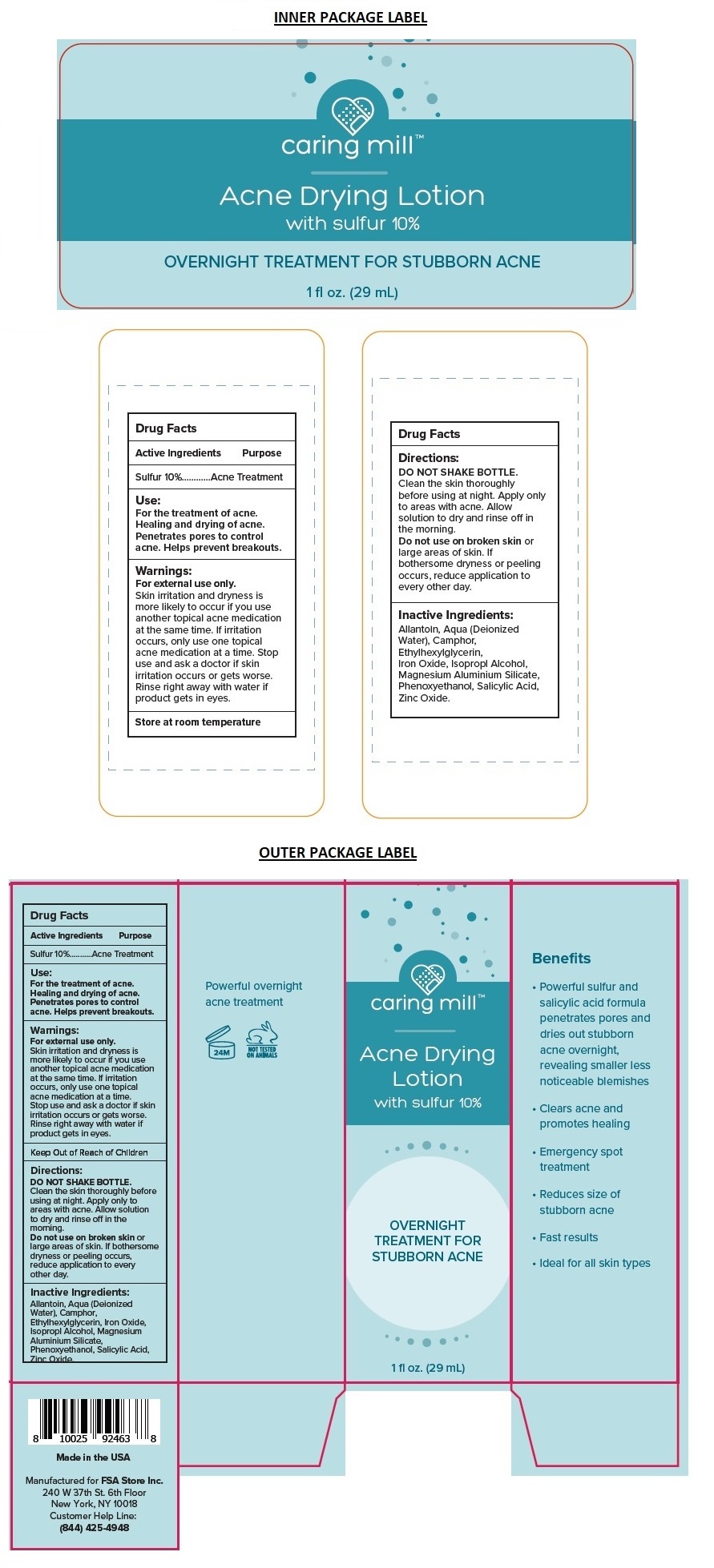 DRUG LABEL: caring mill Acne Drying
NDC: 71328-060 | Form: LOTION
Manufacturer: Clixit, Llc
Category: otc | Type: HUMAN OTC DRUG LABEL
Date: 20210621

ACTIVE INGREDIENTS: SULFUR 100 mg/1 mL
INACTIVE INGREDIENTS: ALLANTOIN; WATER; CAMPHOR (SYNTHETIC); ETHYLHEXYLGLYCERIN; FERRIC OXIDE RED; ISOPROPYL ALCOHOL; MAGNESIUM ALUMINUM SILICATE; PHENOXYETHANOL; SALICYLIC ACID; ZINC OXIDE

caring mill™ Acne Drying Lotion

Active Ingredients

Sulfur 10%

Purpose

Acne Treatment

Use:

For the treatment of acne. Healing and drying of acne. Penetrates pores to control acne. Helps prevent breakouts.

Warnings:

For external use only.
Skin irritation and dryness is more likely to occur if you use another topical acne medication at the same time. If irritation occurs, only use one topical acne medication at a time. Stop use and ask a doctor if skin irritation occurs or gets worse. Rinse right away with water if product gets in eyes.

Keep out of reach of children.

Directions:

DO NOT SHAKE BOTTLE.
Clean the skin thoroughly before using at night. Apply only to areas with acne. Allow solution to dry and rinse off in the morning.

Do not use on broken skin or large areas of skin. If bothersome dryness or peeling occurs, reduce application to every other day.

Inactive Ingredients:

Allantoin, Aqua (Deionized Water), Camphor, Ethylhexylglycerin, Iron Oxide, Isopropyl Alcohol, Magnesium Aluminium Silicate, Phenoxyethanol, Salicylic Acid, Zinc Oxide.

STORAGE AND HANDLING

Store at room temperature.

OVERNIGHT TREATMENT FOR STUBBORN ACNE

Benefits

• Powerful sulfur and salicylic acid formula penetrates pores and dries out stubborn acne overnight, revealing smaller less noticeable blemishes.

• Clears acne and promotes healing

• Emergency spot treatment

• Reduces size of stubborn acne

• Fast results

• Ideal for all skin types

Powerful overnight acne treatment

NOT TESTED ON ANIMALS

Made in the USA

Manufactured for FSA Store Inc.
240 W 37th St. 6th Floor
New York, NY 10018
Customer Help Line:
(844) 425-4948